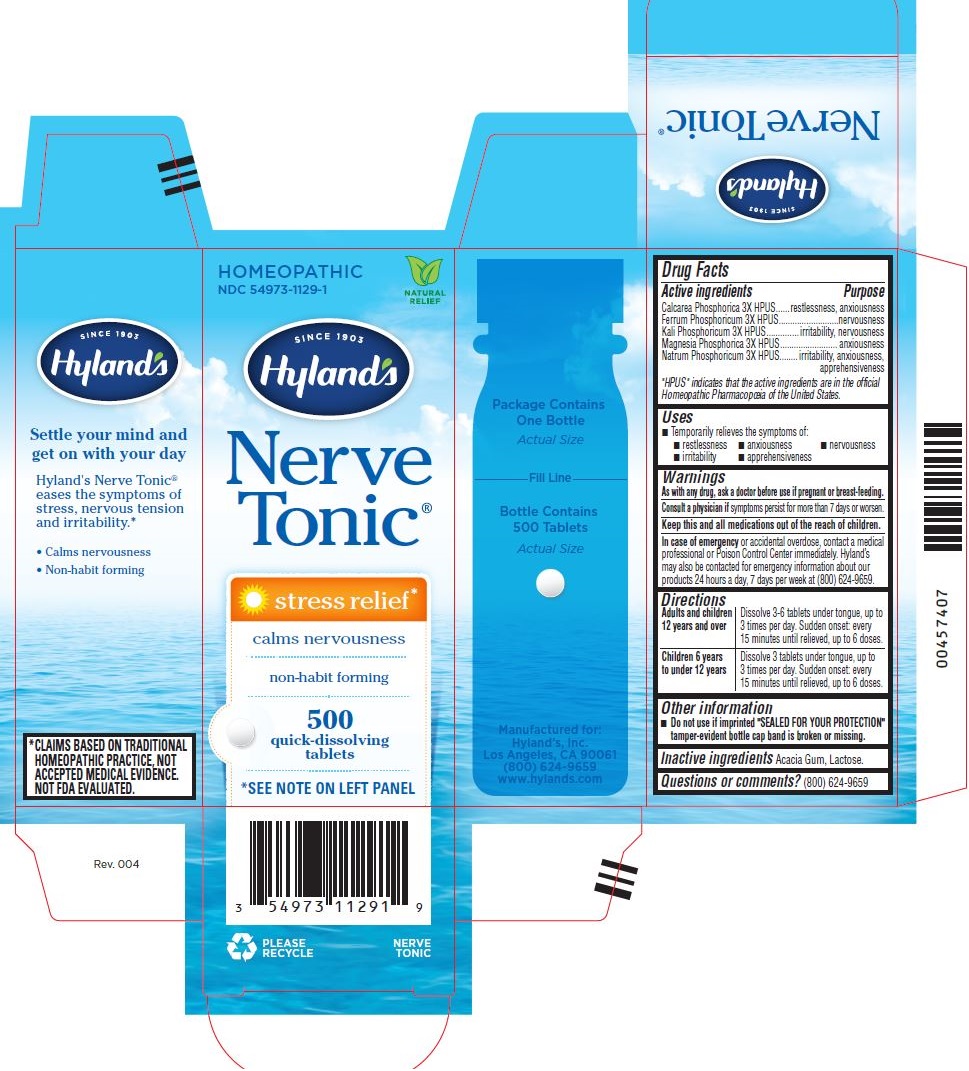 DRUG LABEL: NERVE TONIC STRESS RELIEF
NDC: 54973-1129 | Form: TABLET
Manufacturer: Hyland's Inc.
Category: homeopathic | Type: HUMAN OTC DRUG LABEL
Date: 20221213

ACTIVE INGREDIENTS: CALCIUM PHOSPHATE 3 [hp_X]/1 1; IRON 3 [hp_X]/1 1; POTASSIUM PHOSPHATE, UNSPECIFIED FORM 3 [hp_X]/1 1; MAGNESIUM PHOSPHATE, DIBASIC TRIHYDRATE 3 [hp_X]/1 1; SODIUM PHOSPHATE 3 [hp_X]/1 1
INACTIVE INGREDIENTS: LACTOSE; ACACIA

Nerve Tonic Stress Relief

Drug Facts

Active ingredients

Active ingredients | Purpose
Calcarea Phosphorica 3X HPUS | restlessness, anxiousness
Ferrum Phosphoricum 3X HPUS | nervousness
Kali Phosphoricum 3X HPUS | irritability,nervousness
Magnesia Phosphorica 3X HPUS | anxiousness
Natrum Phosphoricum 3X HPUS | irritability, anxiousness apprehensiveness

“HPUS” indicates that the active ingredients are in the official Homeopathic Pharmacopoeia of the United States.

Uses

■ Temporarily relieves the symptoms of:

■ restlessness ■ anxiousness ■nervousness

■ irritability ■ apprehensiveness

Warnings

PREGNANCY OR BREAST FEEDING

As with any drug, ask a doctor before use if pregnant or breast-feeding.

ASK DOCTOR

Consult a physician if symptoms persist for more than 7 days or worsen.

KEEP OUT OF REACH OF CHILDREN

Keep this and all medications out of the reach of children.

OVERDOSAGE

In case of emergency or accidental overdose, contact a medical professional or Poison Control Center immediately. Hyland’s may also be contacted for emergency information about our products 24 hours a day, 7 days per week at (800) 624-9659.

Directions

Adults & children 12 years and over

Dissolve 3-6 tablets under tongue, up to 3 times per day. Sudden onset: every 15 minutes until relieved, up to 6 doses.

Children 6 years to under 12 years

Dissolve 3 tablets under tongue, up to 3 times per day. Sudden onset: every 15 minutes until relieved, up to 6 doses.

Other information

■ Do not use if imprinted "SEALED FOR YOUR PROTECTION" tamper-evident bottle cap band is broken or missing.

Inactive Ingredients

Acacia Gum, Lactose.

Questions or comments?

(800) 624-9659

PURPOSE

stress relief, calms nervousness

Indications and Usage

Uses

■ Temporarily relieves the symptoms of:

■ restlessness ■ anxiousness ■nervousness

■ irritability ■ apprehensiveness

PRINCIPAL DISPLAY PANEL - 500 Tablet Bottle Carton

HOMEOPATHIC

NDC 54973-1129-1

Natural

Relief

SINCE 1903

Hyland's

Nerve

Tonic®

stress relief*

calms nervousness

non-habit forming

500
quick-dissolving

tablets

*SEE NOTE ON LEFT PANEL